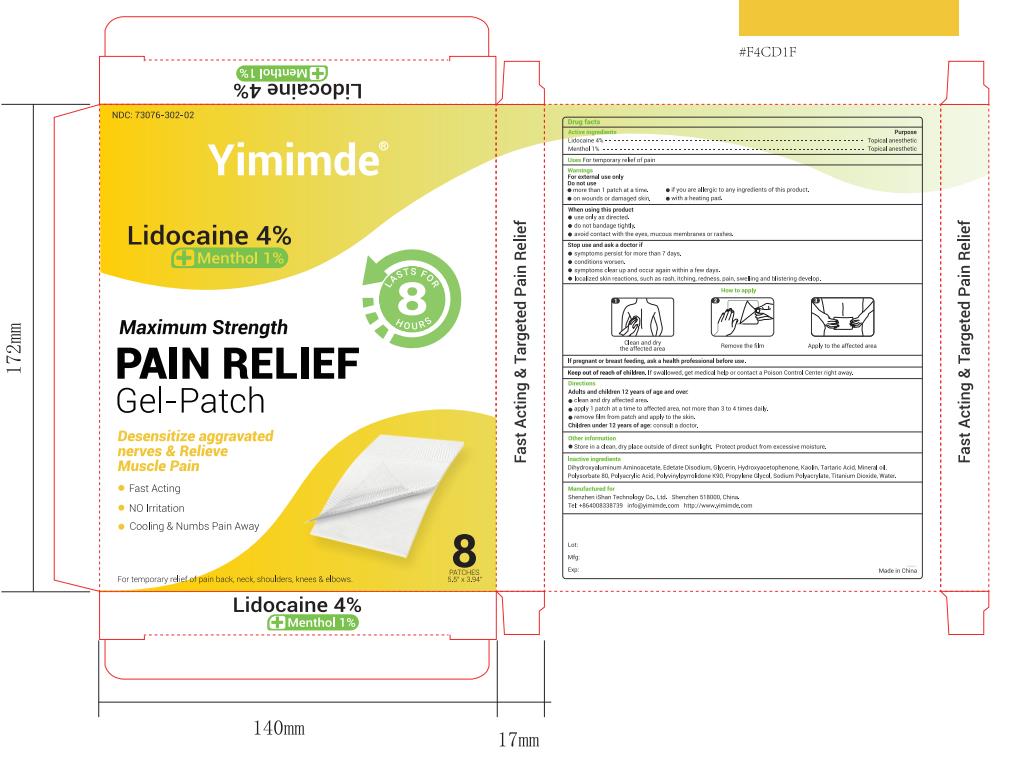 DRUG LABEL: Yimimde PAIN RELIEF Gel-Patch
NDC: 73076-302 | Form: PATCH
Manufacturer: Shenzhen Ishan Technology Co., Ltd
Category: homeopathic | Type: HUMAN OTC DRUG LABEL
Date: 20260212

ACTIVE INGREDIENTS: MENTHOL 1 g/100 g; LIDOCAINE 4 g/100 g
INACTIVE INGREDIENTS: MINERAL OIL; HYDROXYACETOPHENONE; POLYACRYLIC ACID (250000 MW); POLYSORBATE 80; TARTARIC ACID; GLYCERIN; POVIDONE K90; TITANIUM DIOXIDE; PROPYLENE GLYCOL; EDETATE DISODIUM; SODIUM POLYACRYLATE (2500000 MW); WATER; ALUMINUM GLYCINATE; KAOLIN

Inactive Ingredients

Water, Dihydroxyaluminum Aminoacetate, Glycerol, Kaolin, Methylparaben, Polyacrylic Acid, Polysorbate80 Povidone K90 Propylene Glycol, Propylparaben, Sodium Polyacrylate, Tartaric Acid, Titanium Dioxide.

Active ingredients

Active ingredients Purpose Lidocaine 4%---Topical anesthetic

Menthol 1%---Topical anesthetic

Keep out of reach of children

if swallowed, call poison control or seek medical help.

Ask a doctor

before using on children under 2 years of age.

Stop use

Stop use and ask a doctor if ● symptoms persist for more than 7 days
● conditions worsen.
● symptoms clear up and occur again within a few days. ● localized skin reactions, such as rash, itching, rednesspain, swelling and blistering develop.

Uses

For temporary relief of pain.

Other information

Store in a clean, dry place outside of direct sunlight. Protect productfrom excessive moisture.

Directions

Adults and children 12 years of age and over: ● clean and dry affected area.
● apply 1 patch at a time to affected area, not morethan 3 to 4 times daily. ● remove film from patch and apply to the skin. Children under 12 years of age: consult a doctor

When using this product * use only as directed.

* do not bandage tightly.
* avoid contact with the eyes, mucous membranes or rashes.

Warnings

For external use only
Do not use
* more than 1 patch at a time.
* on wounds, damaged skin or with a heating pad.
* if you are allergic to any ingredients of this product.